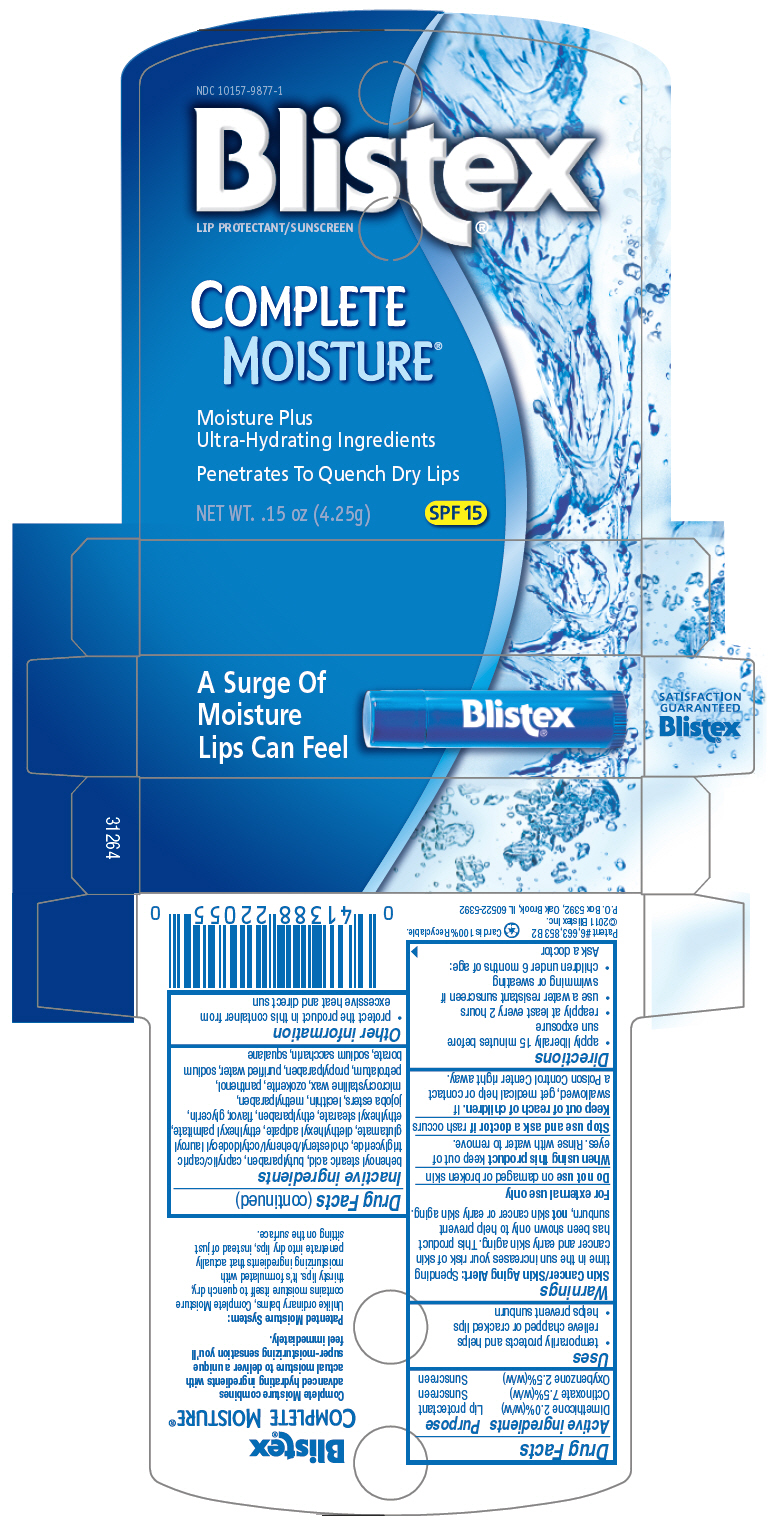 DRUG LABEL: Blistex 
NDC: 10157-9877 | Form: STICK
Manufacturer: Blistex Inc.
Category: otc | Type: HUMAN OTC DRUG LABEL
Date: 20131112

ACTIVE INGREDIENTS: Octinoxate 7.5 g/100 g; Oxybenzone 2.5 g/100 g; Dimethicone 2 g/100 g
INACTIVE INGREDIENTS: DIETHYLHEXYL ADIPATE; PROPYLPARABEN; BUTYLPARABEN; ETHYLPARABEN; METHYLPARABEN; water; saccharin sodium; squalane; panthenol; microcrystalline wax; glycerin; ETHYLHEXYL STEARATE; ETHYLHEXYL PALMITATE; MEDIUM-CHAIN TRIGLYCERIDES; petrolatum; 7-BEHENOYLSTEARIC ACID; SODIUM BORATE; CHOLESTERYL/BEHENYL/OCTYLDODECYL LAUROYL GLUTAMATE; ceresin

Blistex®
Complete Moisture®

Drug Facts

ACTIVE INGREDIENT

Active ingredients | Purpose
Dimethicone 2.0%(w/w) | Lip protectant
Octinoxate 7.5%(w/w) | Sunscreen
Oxybenzone 2.5%(w/w) | Sunscreen

Uses

- temporarily protects and helps relieve chapped or cracked lips
- helps prevent sunburn

Warnings

Skin Cancer/Skin Aging Alert

Spending time in the sun increases your risk of skin cancer and early skin aging. This product has been shown only to help prevent sunburn, not skin cancer or early skin aging.

For external use only

Do not use on damaged or broken skin

When using this product keep out of eyes. Rinse with water to remove.

Stop use and ask a doctor if rash occurs

Keep out of reach of children. If swallowed, get medical help or contact a Poison Control Center right away.

Directions

- apply liberally 15 minutes before sun exposure
- reapply at least every 2 hours
- use a water resistant sunscreen if swimming or sweating
- children under 6 months of age: Ask a doctor

Inactive ingredients

behenoyl stearic acid, butylparaben, caprylic/capric triglyceride, cholesteryl/behenyl/octyldodecyl lauroyl glutamate, diethylhexyl adipate, ethylhexyl palmitate, ethylhexyl stearate, ethylparaben, flavor, glycerin, jojoba esters, lecithin, methylparaben, microcrystalline wax, ozokerite, panthenol, petrolatum, propylparaben, purified water, sodium borate, sodium saccharin, squalane

Other information

- protect the product in this container from excessive heat and direct sun

PRINCIPAL DISPLAY PANEL - 4.25g Cylinder Carton

NDC 10157-9877-1

Blistex®
LIP PROTECTANT/SUNSCREEN

COMPLETE
MOISTURE®

Moisture Plus
Ultra-Hydrating Ingredients

Penetrates To Quench Dry Lips

NET WT. .15 oz (4.25g)

SPF 15